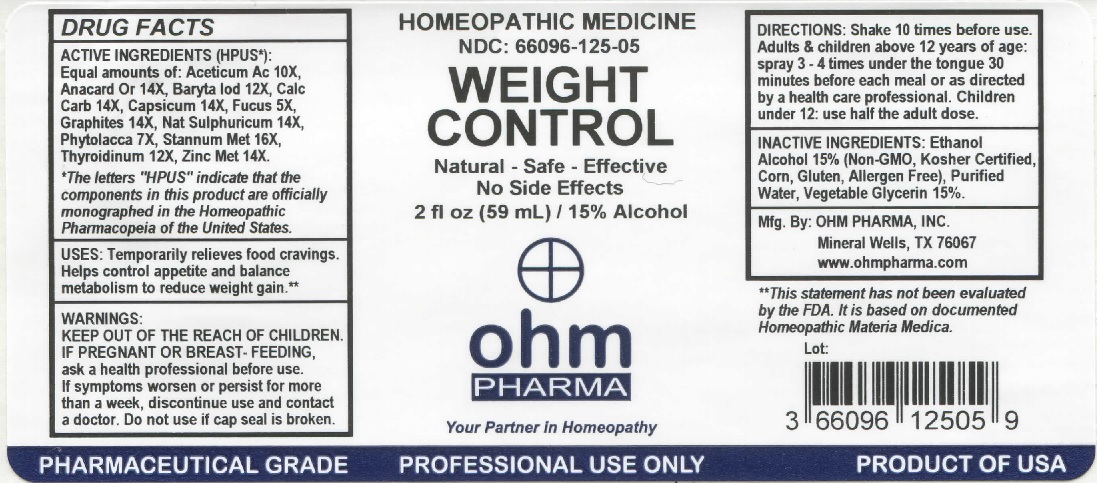 DRUG LABEL: Weight Control
NDC: 66096-125 | Form: SPRAY
Manufacturer: OHM PHARMA INC.
Category: homeopathic | Type: HUMAN OTC DRUG LABEL
Date: 20211229

ACTIVE INGREDIENTS: ACETIC ACID 10 [hp_X]/1 mL; SEMECARPUS ANACARDIUM JUICE 14 [hp_X]/1 mL; BARIUM IODIDE 12 [hp_X]/1 mL; OYSTER SHELL CALCIUM CARBONATE, CRUDE 14 [hp_X]/1 mL; CAPSICUM 14 [hp_X]/1 mL; FUCUS VESICULOSUS 5 [hp_X]/1 mL; GRAPHITE 14 [hp_X]/1 mL; SODIUM SULFATE 14 [hp_X]/1 mL; PHYTOLACCA AMERICANA ROOT 7 [hp_X]/1 mL; TIN 16 [hp_X]/1 mL; THYROID, UNSPECIFIED 12 [hp_X]/1 mL; ZINC 14 [hp_X]/1 mL
INACTIVE INGREDIENTS: ALCOHOL; WATER; GLYCERIN

OHM WEIGHT CONTROL

ACTIVE INGREDIENT

ACTIVE INGREDIENTS (HPUS*): Aceticum Ac 10X, Anacard Or 14X, Baryta Iod 12X, Calc Carb 14X, Capsicum 14X, Fucus 5X, Graphites 14X, Nat Sulphuricum 14X, Phytolacca 7X, Stannum Met 16X, Thyroidinum 12X, Zinc Met 14X.

* The letters "HPUS" indicate that the components in this product are officially monographed in the Homeopathic Pharmacopeia of the United States.

INDICATIONS AND USAGE

USES: Temporarily relieves food cravings. Helps control appetite and balance metabolism to reduce weight gain.

**This statement has not been evaluated by the FDA. It is based on documented Homeopathic Materia Medica.

WARNINGS

WARNINGS: IF PREGNANT OR BREAST - FEEDING, ask a health professional before use. If symptoms worsen or persist for more than a week, discontinue use and contact a doctor.

- KEEP OUT OF THE REACH OF CHILDREN.

DOSAGE AND ADMINISTRATION

DIRECTIONS: Shake 10 times before use. Adults and children above 12 years of age: spray 3-4 times under the tongue 30 minutes before each meal or as directed by a health care professional. Children under 12: use half the adult dose.

Do not use if cap seal is broken.

INACTIVE INGREDIENT

INACTIVE INGREDIENTS: Ethanol Alcohol 15% (Non-GMO, Kosher Certified, Corn, Gluten, Allergen Free), Purified Water, Vegetable Glycerin 15%.

QUESTIONS

Mfg. By: OHM PHARMA, INC. Mineral Wells, TX 76067

www.ohmpharma.com

PACKAGE LABEL

HOMEOPATHIC MEDICINE
NDC: 66096-125-05
WEIGHT CONTROL
Natural - Safe - Effective
No Side Effects
2 fl oz (59 mL) / 15% Alcohol

PRODUCT OF USA

PURPOSE

Weight Control